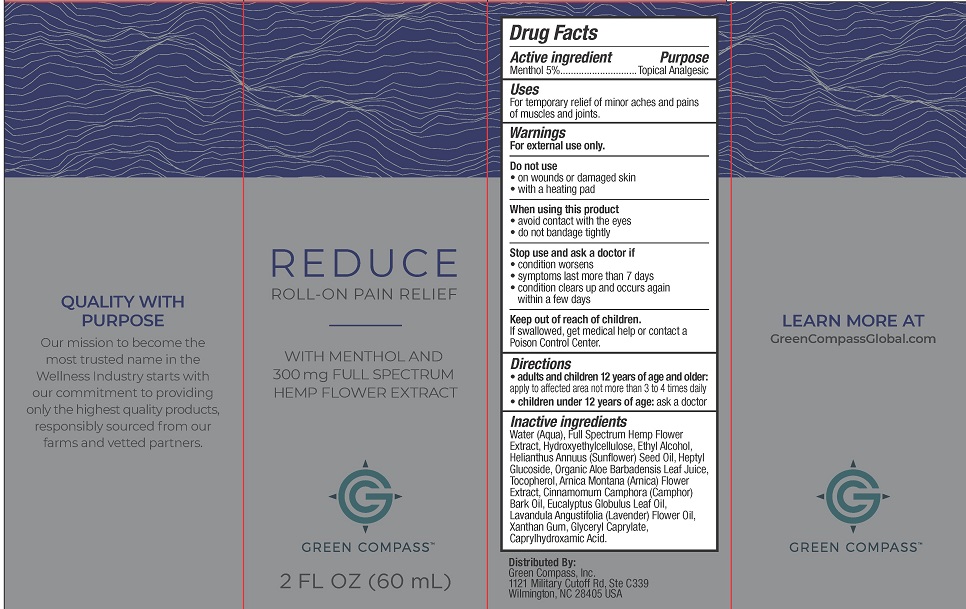 DRUG LABEL: Green Compass Reduce Roll-On Pain Relief
NDC: 73132-003 | Form: LIQUID
Manufacturer: Green Compass, Inc.
Category: otc | Type: HUMAN OTC DRUG LABEL
Date: 20250101

ACTIVE INGREDIENTS: MENTHOL, UNSPECIFIED FORM 5 g/100 mL
INACTIVE INGREDIENTS: XANTHAN GUM; ARNICA MONTANA; HEPTYL GLUCOSIDE; HYDROXYETHYL CELLULOSE, UNSPECIFIED; .ALPHA.-TOCOPHEROL ACETATE; CANNABIS SATIVA FLOWERING TOP; SUNFLOWER OIL; GLYCERYL CAPRYLATE; ALCOHOL; CAPRYLHYDROXAMIC ACID; ALOE VERA LEAF; EUCALYPTUS OIL; LAVENDER OIL; WATER; CAMPHOR OIL

Green Compass Reduce Roll-On Pain Relief

Drug Facts

Active ingredient

Menthol 5%

Purpose

Topical Analgesic

Uses

For temporary relief of minor aches and pains of muscles and joints.

Warnings

For external use only.

Do not use

- on wounds or damaged skin
- with a heating pad

When using this product

- avoid contact with the eyes
- do not bandage tightly

Stop use and ask a doctor if

- condition worsens
- symptoms last more than 7 days
- condition clears up and occurs again within a few days

Keep out of reach of children. If swallowed, get medical help or contact a Poison Control Center right away.

Directions

- adults and children 12 years of age and older: apply to affected area not more than 3 to 4 times daily
- children under 12 years of age: ask a doctor

Inactive ingredients

Water (Aqua), Full Spectrum Hemp Flower Extract, Hydroxyethylcellulose, Ethyl Alcohol, Helianthus Annuus (Sunflower) Seed Oil, Heptyl Glucoside, Organic Aloe Barbadensis Leaf Juice, Tocopherol, Arnica Montana (Arnica) Flower Extract, Cinnamomom Camphora (Camphor) Bark Oil, Lavandula Angustifolia (Lavender) Flower Oil, Xanthan Gum, Glyceryl Caprylate, Caprylhydroxamic Acid.

Distributed By:

Green Compass, Inc.

1121 Military Cutoff Rd., Ste C339

Wilmington, NC 28405 USA

PACKAGE LABEL

REDUCE

ROLL-ON PAIN RELIEF

WITH MENTHOL AND 300 mg FULL SPECTRUM HEMP FLOWER EXTRACT

GREEN COMPASS

2 FL OZ (60 mL)